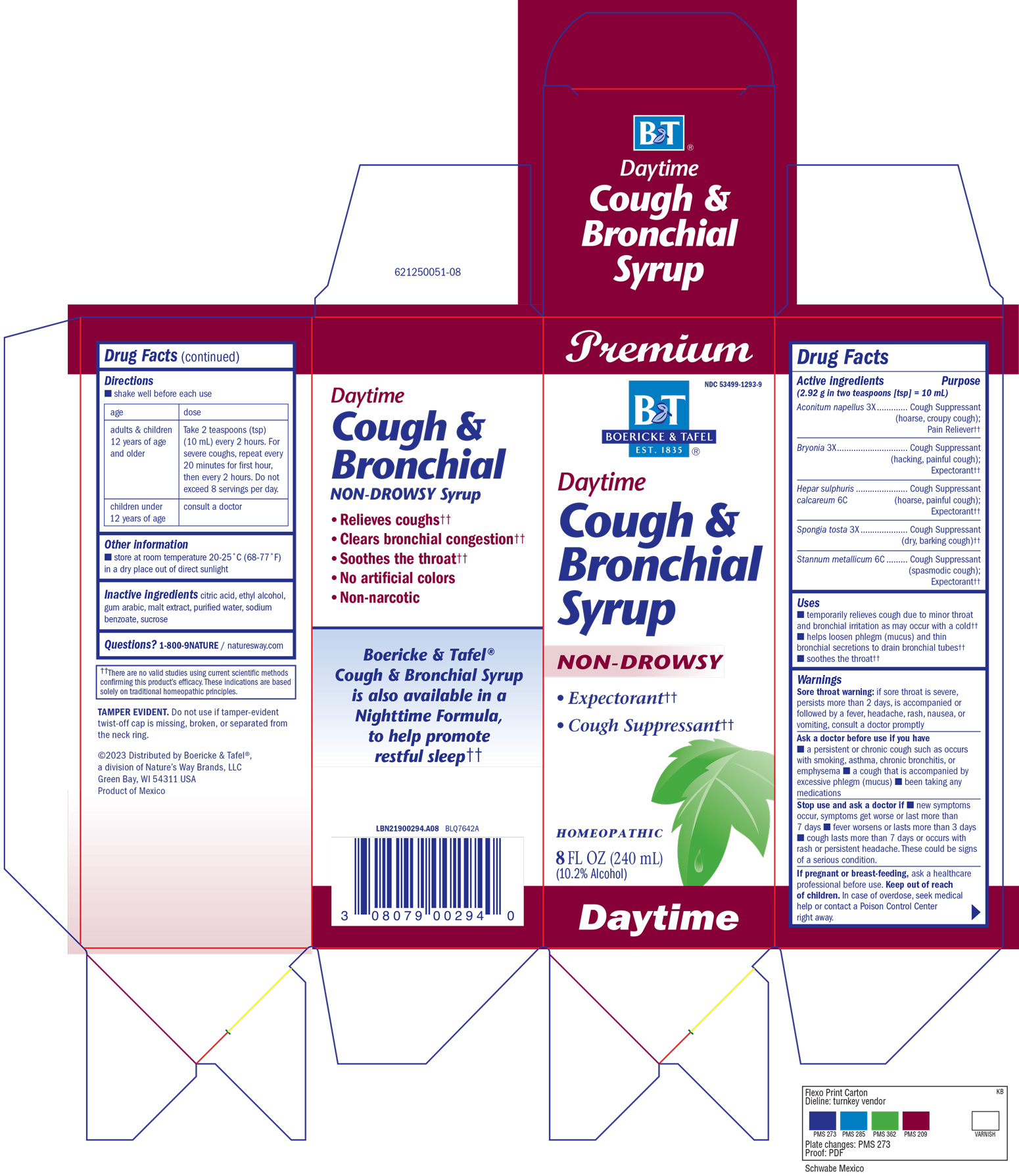 DRUG LABEL: Cough and Bronchial Daytime Syrup
NDC: 68466-1008 | Form: SYRUP
Manufacturer: Schwabe Mexico, S.A. de C.V.
Category: homeopathic | Type: HUMAN OTC DRUG LABEL
Date: 20251208

ACTIVE INGREDIENTS: ACONITUM NAPELLUS 3 [hp_X]/120 mL; BRYONIA ALBA ROOT 3 [hp_X]/120 mL; CALCIUM SULFIDE 6 [hp_C]/120 mL; SPONGIA OFFICINALIS SKELETON, ROASTED 3 [hp_X]/120 mL; TIN 6 [hp_C]/120 mL
INACTIVE INGREDIENTS: ACACIA; BARLEY MALT; WATER; SODIUM BENZOATE; SUCROSE; CITRIC ACID MONOHYDRATE; ALCOHOL

Cough and Bronchial Daytime Syrup

Active Ingredients

Aconitum napellus 3X

Bryonia 3X

Hepar sulphuris calcareum 6C

Spongia tosta 3X

Stannum metallicum 6C

Inactive Ingredient

Citric Acid

Ethyl Alcohol

Gum Arabic

Malt Extract

Purified Water

Sodium Benzoate

Sucrose

Dosage & Administration

Directions:

Shake well before each use.

Adults & children 12 years of age and older: Take 2 teaspoons (tsp) (10mL) every 2 hours. For severe coughs, repeat every 20 minutes for first hour, then every 2 hours. Do not exceed 8 servings per day.

Children under 12 years of age: Consult a doctor.

Indications & Usage

Temporarily relieves cough due to minor throat and bronchial irritation as may occur with a cold.

Helps loosen phlegm (mucus) and thin bronchial secretions to drain bronchial tubes.

Soothes the throat.

Purpose

Temporarily relieves cough due to minor throat and bronchial irritation as may occur with a cold.

Helps loosen phlegm (mucus) and thin bronchial secretions to drain bronchial tubes.

Soothes the throat.

Warnings

Sore throat warning: if sore throat is severe, persists more than 2 days, is accompanied or followed by a fever, headache, rash, nausea, or vomiting, consult a doctor promptly.

Ask Doctor

Ask a doctor before use if you have a persistent or chronic cough such as occurs with smoking, asthma, chronic bronchitis, or emphysema; a cough that is accompanied by excessive phlegm (mucus); been taking any medications.

Stop Use

Stop use and ask a doctor if new symptoms occur, symptoms get worse or last more than 7 days, fever worsens or lasts more than 3 days, cough lasts more than 7 days or occurs with rash or persisitent headache.

These could be signs of a serious condition.

Pregnancy or Breast Feeding

If pregnant or breast-feeding, ask a healthcare professional before use.

Keep out of reach of children

Overdose

In case of overdose, seek medical help or contact a Poison Control Center right away.